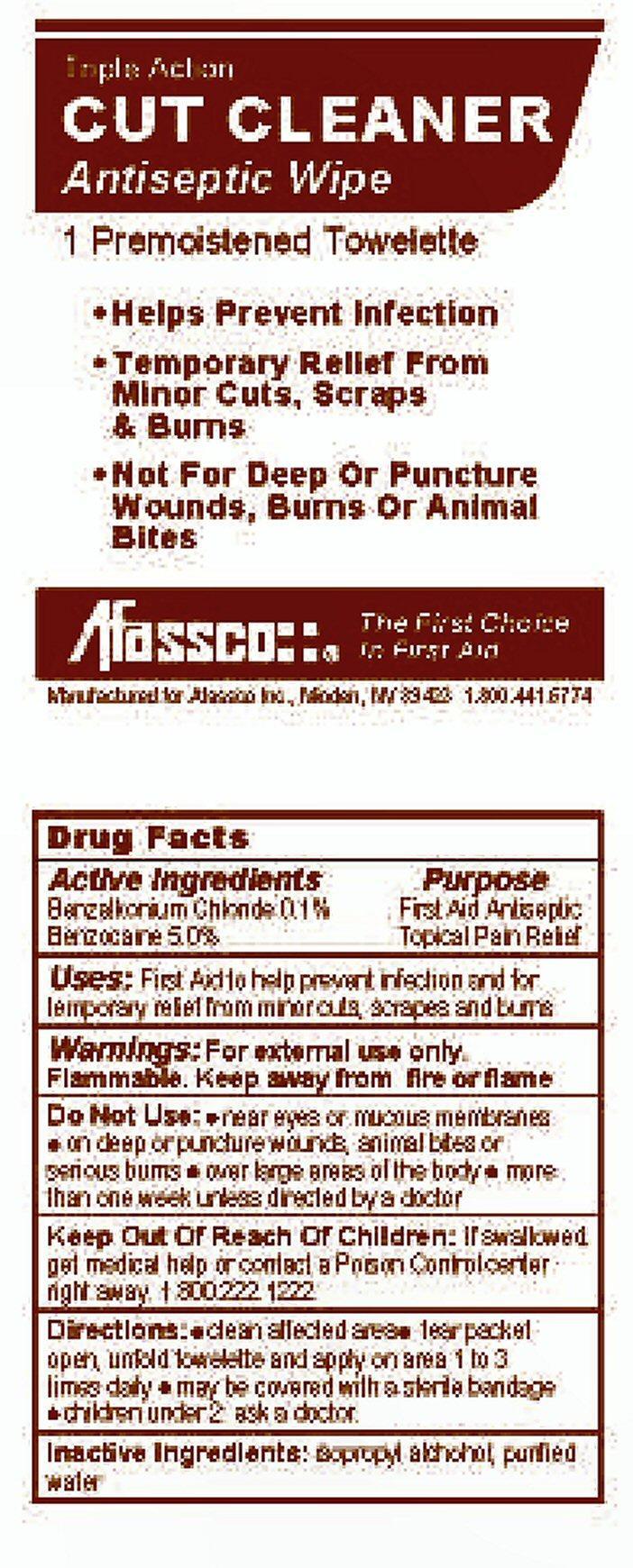 DRUG LABEL: CUT CLEANER
NDC: 51532-4616 | Form: SWAB
Manufacturer: Afassco Inc
Category: otc | Type: HUMAN OTC DRUG LABEL
Date: 20191223

ACTIVE INGREDIENTS: BENZALKONIUM CHLORIDE 0.45 mg/0.45 g; BENZOCAINE 22.5 mg/0.45 g
INACTIVE INGREDIENTS: ISOPROPYL ALCOHOL; WATER

Drug Facts

Benzalkonium Chloride 0.1%

Benzocaine 5.0%

Purpose

First Aid Antiseptic

Topical Pain Relief

Keep Out Of Reach Of Children:

If swallowed, get medical help or contact a Poison Control center right away. 1.800.222.1222

Uses:

First Aid to help prevent infection and for temporary relief from minor cuts, scrapes and burns

Warnings:

For external use only.

Flammable. Keep away from fire or flame

Directions:

- clear affected area
- tear packet open, unfold towelette and apply on area 1 to 3 times daily
- maybe covered with a sterile bandage
- children under 2 ask a doctor

Do Not Use:

- near eyes or mucous membranes
- on deep or puncture wounds, animal bites or serious burns
- over large areas of the body
- more than one week unless directed by a doctor

Inactive Ingredients:

isopropyl alcohol. purified water

Product Label CUT CLEANER

CUT CLEANER
Triple Action Antiseptic Wipe

1 Premoistened Towelette

Afassco::® The First Choice In First Aid
Manufactured for Afassco Inc, Minden, NV 89423 1.800.441.6774

- Helps Prevent Infection
- Temporary Relief From Minor Cuts, Scrapes And Burns
- Not For Deep Or Puncture Wounds, Burns OR Animal Bites